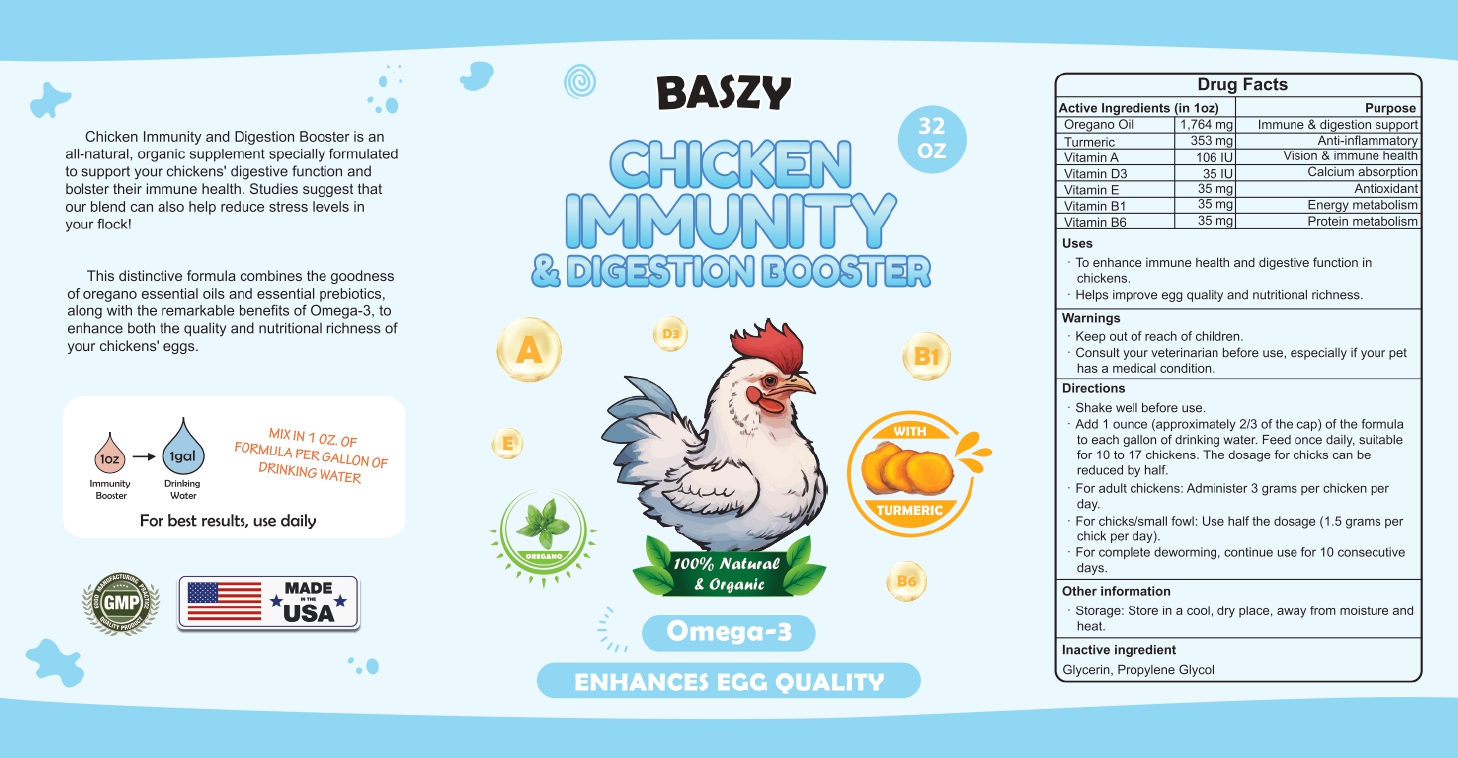 DRUG LABEL: Baszy Chicken Immunity and Digestion Booster Omega 3
NDC: 86202-0001 | Form: SOLUTION/ DROPS
Manufacturer: AMBIENCE FAMILY INC
Category: animal | Type: OTC ANIMAL DRUG LABEL
Date: 20241101

ACTIVE INGREDIENTS: OREGANO LEAF OIL 1764 mg/28 g; TURMERIC 353 mg/28 g; VITAMIN A 106 [iU]/28 g; VITAMIN D3 RECEPTOR 35 [iU]/28 g
INACTIVE INGREDIENTS: VITAMIN E POLYETHYLENE GLYCOL SUCCINATE; GLYCERIN; PROPYLENE GLYCOL

Baszy Chicken Immunity and Digestion Booster

Directions

Shake well before use.

Add 1 ounce (approximately 2/3 of the cap) of the formula 10 each gallon of drinking water. Feed once daily, suitable

for 10 to 17 chickens. The dosage for chicks can be reduced by half.

For adult chickens: Administer 3 grams per chicken per day.

For chicks/small fowl: Use half the dosage (1.5 grams per chick per day).

For complete deworming, continue use for 10 consecutive days.

Storage: Store in a cool, dry place, away from moisture and Heat.

WARNINGS AND PRECAUTIONS

Not for use in humans. Keep out of reach of children. Protective gloves should be used and care should be taken
when handling the product to avoid skin and eye exposure and accidental ingestion. Accidental exposure may result
in skin and eye irritation. Accidental ingestion may cause gastrointestinal disturbances and hypersensitivity reactions
in humans.

PACKAGE LABEL

Content of Labling

Chicken Immunity and Digestion Booster is an all-natural, organic supplement specially formulated to support your chickens' digestive function and bolster their immune health. Studies suggest that our blend can also help reduce stress levels in your flock!
This distinctive formula combines the goodness of oregano essential oils and essential prebiotics, along with the remarkable benefits of Omega-3, to enhance both the quality and nutritional richness of your chickens' eggs.
CHICKEN IMMUNITY
& DIGESTIÓN BOOSTER

TURMERIC
OREGANO

Omega-3

ENHANCES EGG QUALITY
Purpose Immune & digestion support
Anti-inflammatory
Vision & immune health Calcium absorption
Antioxidant Energy metabolism
Protein metabolism
To enhance immune health and digestive function in chickens.
Helps improve egg quality and nutritional richness.